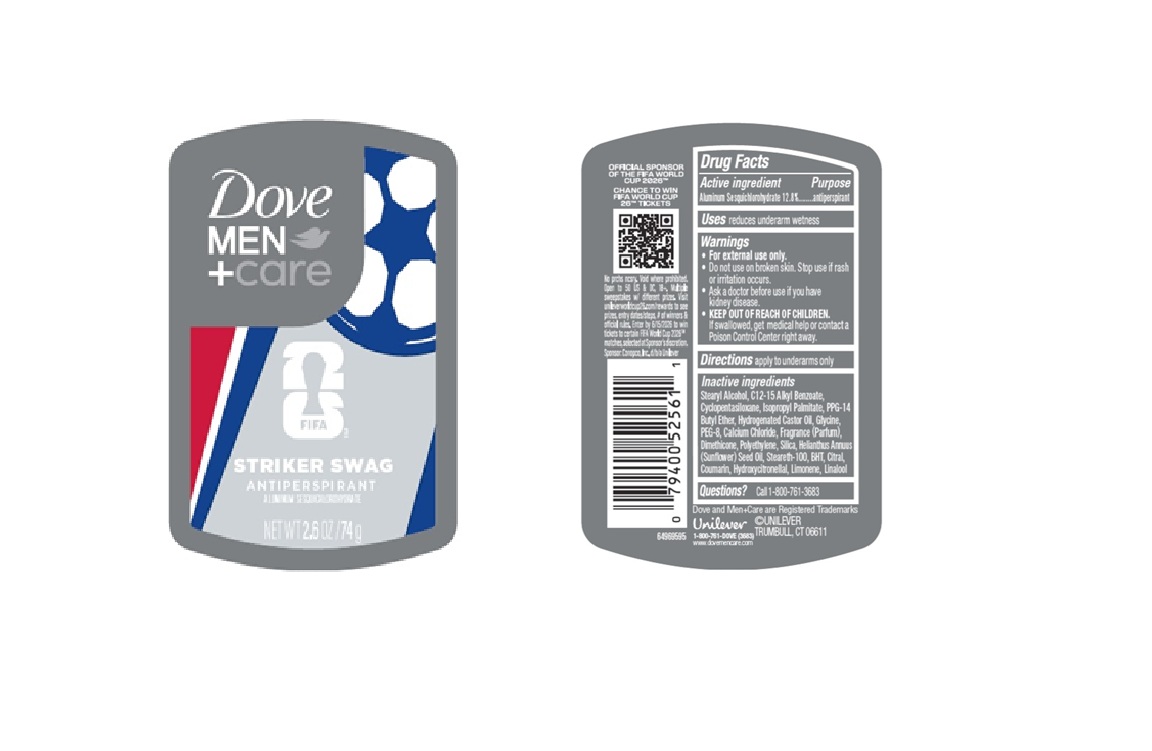 DRUG LABEL: Dove Men Care
NDC: 64942-2411 | Form: STICK
Manufacturer: Conopco d/b/a Unilever
Category: otc | Type: HUMAN OTC DRUG LABEL
Date: 20251209

ACTIVE INGREDIENTS: ALUMINUM SESQUICHLOROHYDRATE 12.8 g/100 g
INACTIVE INGREDIENTS: ISOPROPYL PALMITATE; DIMETHICONE; CALCIUM CHLORIDE; STEARYL ALCOHOL; POLYETHYLENE; GLYCINE; STEARETH-100; BHT; COUMARIN; LIMONENE, (+)-; PPG-14 BUTYL ETHER; LINALOOL; PEG-8; HELIANTHUS ANNUUS (SUNFLOWER) SEED OIL; SILICA; CITRAL; C12-15 ALKYL BENZOATE; CYCLOPENTASILOXANE; HYDROGENATED CASTOR OIL; HYDROXYCITRONELLAL

Dove Men + Care Fifa Striker Swag Antiperspirant Stick

DESCRIPTION

Dove Men + Care Fifa All Star Comfort Antiperspirant Stick

ACTIVE INGREDIENT

Aluminum Sesquichlorohydrate 12.8%

PURPOSE

Antiperspirant

INDICATIONS AND USAGE

reduces underarm wetness

WARNINGS

• For external use only.
•Do not use on broken skin. Stop use if rash or irritation occurs.
•Ask a doctor before use if you have kidney disease.
•If swallowed, get medical help or contact a Poison Control Center right away.

• KEEP OUT OF REACH OF CHILDREN.

DOSAGE AND ADMINISTRATION

apply to underarms only

INACTIVE INGREDIENT

Stearyl Alcohol, C12-15 Alkyl Benzoate, Cyclopentasiloxane, Isopropyl Palmitate, PPG-14 Butyl Ether, Hydrogenated Castor Oil, Glycine, PEG-8, Calcium Chloride, Fragrance (Parfum), Dimethicone, Polyethylene, Silica, Helianthus Annuus (Sunflower) Seed Oil, Steareth-100, BHT, Citral, Coumarin, Hydroxycitronellal, Limonene, Linalool

QUESTIONS

Call 1-800-761-3683